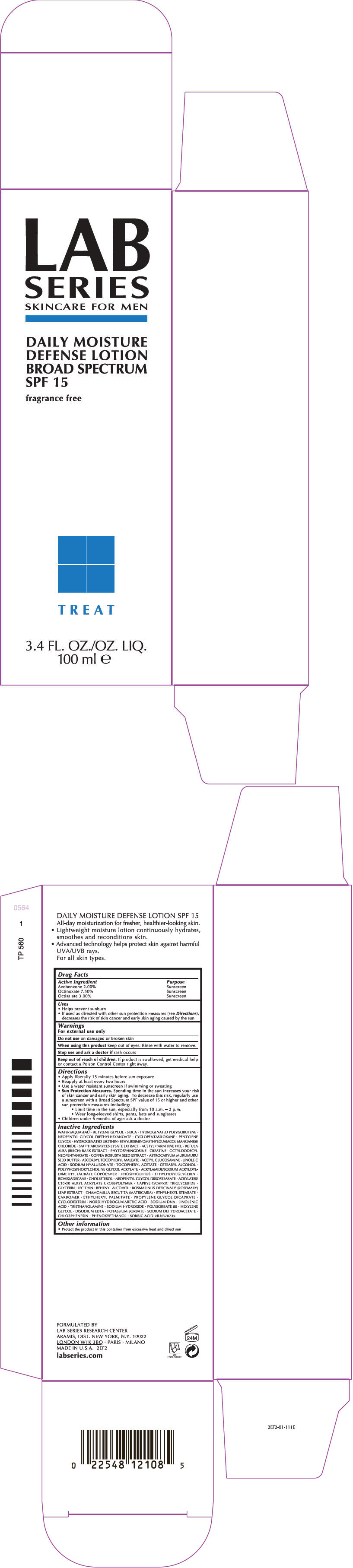 DRUG LABEL: LAB SERIES SKINCARE FOR MEN DAILY MOISTURE DEFENSE BROAD SPECTRUM SPF 15
NDC: 42472-887 | Form: LOTION
Manufacturer: ARAMIS INC.
Category: otc | Type: HUMAN OTC DRUG LABEL
Date: 20181207

ACTIVE INGREDIENTS: AVOBENZONE 0.0212 g/100 mL; OCTINOXATE 0.0795 g/100 mL; OCTISALATE 0.0318 g/100 mL
INACTIVE INGREDIENTS: WATER; BUTYLENE GLYCOL; SILICON DIOXIDE; NEOPENTYL GLYCOL DIETHYLHEXANOATE; CYCLOMETHICONE 5; PENTYLENE GLYCOL; ETHYLBISIMINOMETHYLGUAIACOL MANGANESE CHLORIDE; SACCHAROMYCES LYSATE; ACETYLCARNITINE HYDROCHLORIDE; BETULA PUBESCENS BARK; PHYTOSPHINGOSINE; CREATINE; OCTYLDODECYL NEOPENTANOATE; ROBUSTA COFFEE BEAN; ASTROCARYUM MURUMURU SEED BUTTER; ASCORBYL TOCOPHERYL MALEATE; N-ACETYLGLUCOSAMINE; LINOLEIC ACID; HYALURONATE SODIUM; .ALPHA.-TOCOPHEROL ACETATE; CETOSTEARYL ALCOHOL; ETHYLHEXYLGLYCERIN; ISOHEXADECANE; CHOLESTEROL; NEOPENTYL GLYCOL DIISOSTEARATE; GLYCERIN; DOCOSANOL; ROSEMARY; MATRICARIA CHAMOMILLA; ETHYLHEXYL STEARATE; ETHYLHEXYL PALMITATE; PROPYLENE GLYCOL DICAPRATE; MASOPROCOL; LINOLENIC ACID; TROLAMINE; SODIUM HYDROXIDE; POLYSORBATE 80; HEXYLENE GLYCOL; EDETATE DISODIUM; POTASSIUM SORBATE; SODIUM DEHYDROACETATE; CHLORPHENESIN; PHENOXYETHANOL; SORBIC ACID

LAB SERIES SKINCARE FOR MEN DAILY MOISTURE DEFENSE LOTION BROAD SPECTRUM SPF 15

Drug Facts

ACTIVE INGREDIENT

Active Ingredient | Purpose
Avobenzone 2.00% | Sunscreen
Octinoxate 7.50% | Sunscreen
Octisalate 3.00% | Sunscreen

Uses

- Helps prevent sunburn
- If used as directed with other sun protection measures (see Directions), decreases the risk of skin cancer and early skin aging caused by the sun

Warnings

For external use only

Do not use on damaged or broken skin

When using this product keep out of eyes. Rinse with water to remove.

Stop use and ask a doctor if rash occurs

Keep out of reach of children. If product is swallowed, get medical help or contact a Poison Control Center right away.

Directions

- Apply liberally 15 minutes before sun exposure
- Reapply at least every two hours
- Use a water resistant sunscreen if swimming or sweating
- Sun Protection Measures. Spending time in the sun increases your risk of skin cancer and early skin aging. To decrease this risk, regularly use a sunscreen with a Broad Spectrum SPF value of 15 or higher and other sun protection measures including:
  - Limit time in the sun, especially from 10 a.m. – 2 p.m.
  - Wear long-sleeved shirts, pants, hats and sunglasses
- Children under 6 months of age: ask a doctor

Inactive Ingredients

WATER\AQUA\EAU • BUTYLENE GLYCOL • SILICA • HYDROGENATED POLYISOBUTENE • NEOPENTYL GLYCOL DIETHYLHEXANOATE • CYCLOPENTASILOXANE • PENTYLENE GLYCOL • HYDROGENATED LECITHIN • ETHYLBISIMINOMETHYLGUAIACOL MANGANESE CHLORIDE • SACCHAROMYCES LYSATE EXTRACT • ACETYL CARNITINE HCL • BETULA ALBA (BIRCH) BARK EXTRACT • PHYTOSPHINGOSINE • CREATINE • OCTYLDODECYL NEOPENTANOATE • COFFEA ROBUSTA SEED EXTRACT • ASTROCARYUM MURUMURU SEED BUTTER • ASCORBYL TOCOPHERYL MALEATE • ACETYL GLUCOSAMINE • LINOLEIC ACID • SODIUM HYALURONATE • TOCOPHERYL ACETATE • CETEARYL ALCOHOL • POLYPHOSPHORYLCHOLINE GLYCOL ACRYLATE • ACRYLAMIDE/SODIUM ACRYLOYLDIMETHYLTAURATE COPOLYMER • PHOSPHOLIPIDS • ETHYLHEXYLGLYCERIN • ISOHEXADECANE • CHOLESTEROL • NEOPENTYL GLYCOL DIISOSTEARATE • ACRYLATES/C10-30 ALKYL ACRYLATE CROSSPOLYMER • CAPRYLIC/CAPRIC TRIGLYCERIDE • GLYCERIN • LECITHIN • BEHENYL ALCOHOL • ROSMARINUS OFFICINALIS (ROSEMARY) LEAF EXTRACT • CHAMOMILLA RECUTITA (MATRICARIA) • ETHYLHEXYL STEARATE • CARBOMER • ETHYLHEXYL PALMITATE • PROPYLENE GLYCOL DICAPRATE • CYCLODEXTRIN • NORDIHYDROGUAIARETIC ACID • SODIUM DNA • LINOLENIC ACID • TRIETHANOLAMINE • SODIUM HYDROXIDE • POLYSORBATE 80 • HEXYLENE GLYCOL • DISODIUM EDTA • POTASSIUM SORBATE • SODIUM DEHYDROACETATE • CHLORPHENESIN • PHENOXYETHANOL • SORBIC ACID <ILN37073>

Other information

- Protect the product in this container from excessive heat and direct sun

PRINCIPAL DISPLAY PANEL - 100 ml Tube Carton

LAB
SERIES
SKINCARE FOR MEN

DAILY MOISTURE
DEFENSE LOTION
BROAD SPECTRUM
SPF 15

fragrance free

TREAT

3.4 FL. OZ./OZ. LIQ.
100 ml e